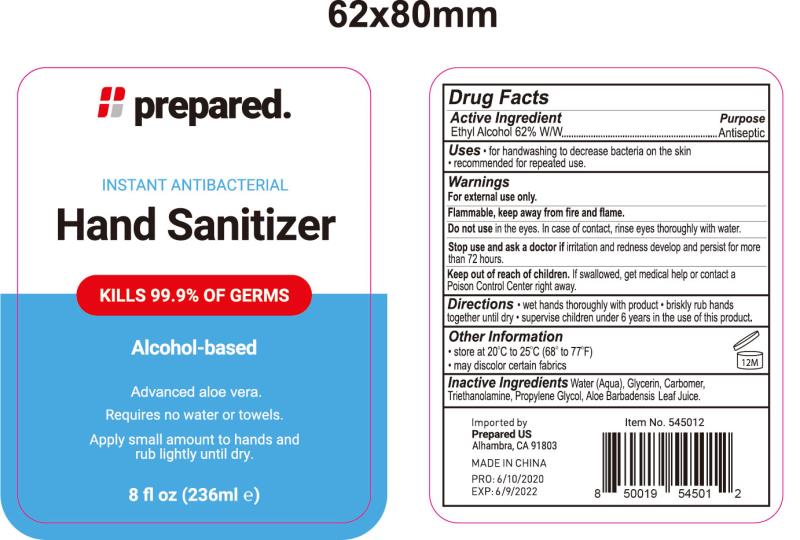 DRUG LABEL: INSTANT ANTIBACTERIAL HAND SANITIZER
NDC: 76681-011 | Form: GEL
Manufacturer: Taizhou Huangyan Delishi Daily Necessity Co., Ltd.
Category: otc | Type: HUMAN OTC DRUG LABEL
Date: 20200608

ACTIVE INGREDIENTS: ALCOHOL 62 mL/100 mL
INACTIVE INGREDIENTS: TROLAMINE; WATER; PROPYLENE GLYCOL; ALOE VERA LEAF; CARBOMER 934

INSTANT ANTIBACTERIAL HAND SANITIZER

Purpose

Antiseptic

Use

. for handwashing to decrease bacteria on the skin

.recommended for repeated use.

Warnings

For external use only. Flammable. Keep away from hear and flame.

Do not use. In the eyes. In case of contact, rinse eyes thoroughly with water.

WHEN USING

/

STOP USE

If irritation or rash occurs. These may be signs of a serious condition.

KEEP OUT OF REACH OF CHILDREN

If swallowed, get medical hep or contact a Poison Control Center right away.

Directions

Wet hands thoroughly with product . briskly rub hands together until dry.

Supervise children under 6 years in theuse of this product.

Other information

Store at 20℃ to 25℃ [68°-77°F]

May discolor certain fabrics

Inactive ingredients

water[Aqua]. Glycerin. Carbomer. Triethanolamine,

Propylene Glycol, Aloe barbadensis Leaf Juice

ACTIVE INGREDIENT

Ethyl Alcohol 62% v/v